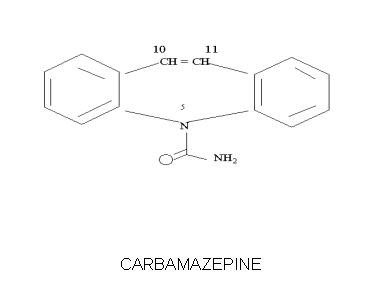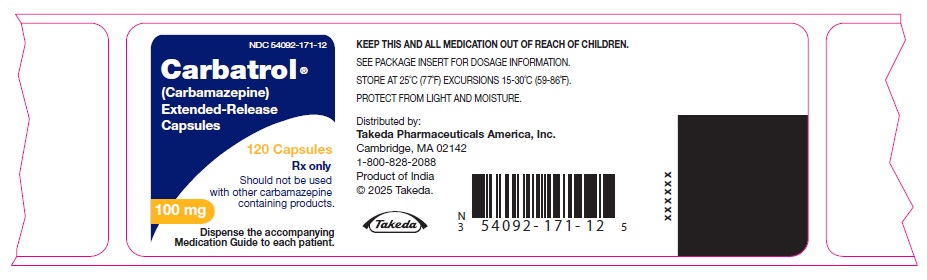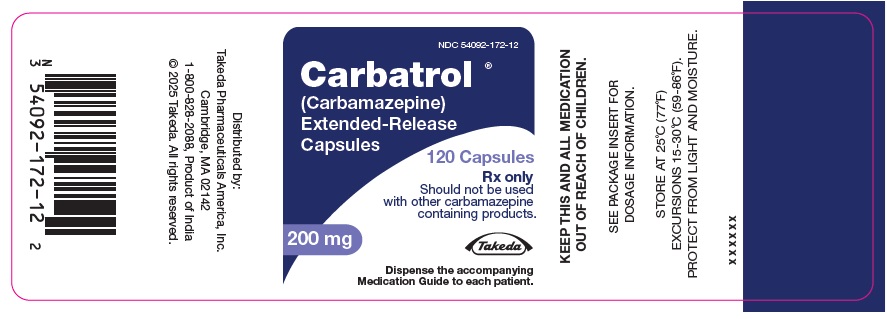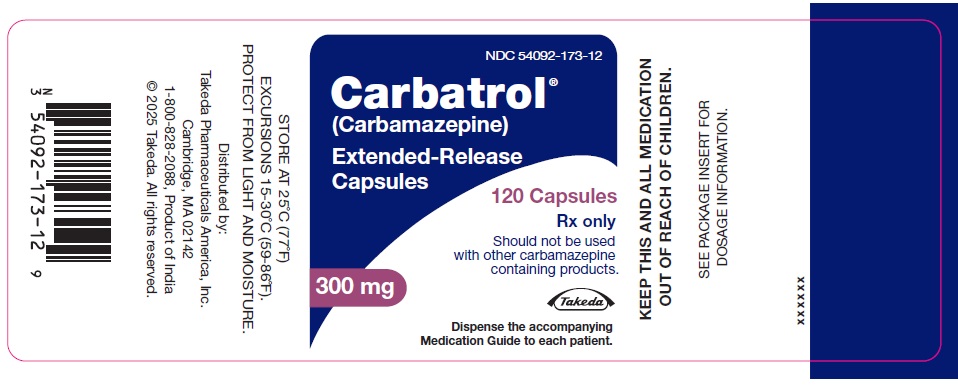 DRUG LABEL: Carbatrol
NDC: 54092-171 | Form: CAPSULE, EXTENDED RELEASE
Manufacturer: Takeda Pharmaceuticals America, Inc.
Category: prescription | Type: HUMAN PRESCRIPTION DRUG LABEL
Date: 20250627

ACTIVE INGREDIENTS: CARBAMAZEPINE 100 mg/1 1
INACTIVE INGREDIENTS: CITRIC ACID MONOHYDRATE; SILICON DIOXIDE; LACTOSE MONOHYDRATE; MICROCRYSTALLINE CELLULOSE; POLYETHYLENE GLYCOL, UNSPECIFIED; POVIDONE, UNSPECIFIED; SODIUM LAURYL SULFATE; TALC; TRIETHYL CITRATE; GELATIN, UNSPECIFIED; FD&C BLUE NO. 2; FERRIC OXIDE YELLOW; TITANIUM DIOXIDE; METHACRYLIC ACID AND ETHYL ACRYLATE COPOLYMER; AMMONIO METHACRYLATE COPOLYMER TYPE A

CARBATROL®
(carbamazepine) Extended-Release Capsules
100 mg, 200 mg and 300 mg
Rx only

WARNING

SERIOUS DERMATOLOGIC REACTIONS AND HLA-B*1502 ALLELE

SERIOUS AND SOMETIMES FATAL DERMATOLOGIC REACTIONS, INCLUDING TOXIC EPIDERMAL NECROLYSIS (TEN) AND STEVENS-JOHNSON SYNDROME (SJS), HAVE BEEN REPORTED DURING TREATMENT WITH CARBAMAZEPINE. THESE REACTIONS ARE ESTIMATED TO OCCUR IN 1 TO 6 PER 10,000 NEW USERS IN COUNTRIES WITH MAINLY CAUCASIAN POPULATIONS, BUT THE RISK IN SOME ASIAN COUNTRIES IS ESTIMATED TO BE ABOUT 10 TIMES HIGHER. STUDIES IN PATIENTS OF CHINESE ANCESTRY HAVE FOUND A STRONG ASSOCIATION BETWEEN THE RISK OF DEVELOPING SJS/TEN AND THE PRESENCE OF HLA-B*1502, AN INHERITED ALLELIC VARIANT OF THE HLA-B GENE. HLA-B*1502 IS FOUND ALMOST EXCLUSIVELY IN PATIENTS WITH ANCESTRY ACROSS BROAD AREAS OF ASIA. PATIENTS WITH ANCESTRY IN GENETICALLY AT-RISK POPULATIONS SHOULD BE SCREENED FOR THE PRESENCE OF HLA-B*1502 PRIOR TO INITIATING TREATMENT WITH CARBATROL®. PATIENTS TESTING POSITIVE FOR THE ALLELE SHOULD NOT BE TREATED WITH CARBATROL UNLESS THE BENEFIT CLEARLY OUTWEIGHS THE RISK (SEE WARNINGS AND PRECAUTIONS/LABORATORY TESTS).

APLASTIC ANEMIA AND AGRANULOCYTOSIS

APLASTIC ANEMIA AND AGRANULOCYTOSIS HAVE BEEN REPORTED IN ASSOCIATION WITH THE USE OF CARBAMAZEPINE. DATA FROM A POPULATION-BASED CASE-CONTROL STUDY DEMONSTRATE THAT THE RISK OF DEVELOPING THESE REACTIONS IS 5-8 TIMES GREATER THAN IN THE GENERAL POPULATION. HOWEVER, THE OVERALL RISK OF THESE REACTIONS IN THE UNTREATED GENERAL POPULATION IS LOW, APPROXIMATELY SIX PATIENTS PER ONE MILLION POPULATION PER YEAR FOR AGRANULOCYTOSIS AND TWO PATIENTS PER ONE MILLION POPULATION PER YEAR FOR APLASTIC ANEMIA.

ALTHOUGH REPORTS OF TRANSIENT OR PERSISTENT DECREASED PLATELET OR WHITE BLOOD CELL COUNTS ARE NOT UNCOMMON IN ASSOCIATION WITH THE USE OF CARBAMAZEPINE, DATA ARE NOT AVAILABLE TO ESTIMATE ACCURATELY THEIR INCIDENCE OR OUTCOME. HOWEVER, THE VAST MAJORITY OF THE CASES OF LEUKOPENIA HAVE NOT PROGRESSED TO THE MORE SERIOUS CONDITIONS OF APLASTIC ANEMIA OR AGRANULOCYTOSIS.

BECAUSE OF THE VERY LOW INCIDENCE OF AGRANULOCYTOSIS AND APLASTIC ANEMIA, THE VAST MAJORITY OF MINOR HEMATOLOGIC CHANGES OBSERVED IN MONITORING OF PATIENTS ON CARBAMAZEPINE ARE UNLIKELY TO SIGNAL THE OCCURRENCE OF EITHER ABNORMALITY. NONETHELESS, COMPLETE PRETREATMENT HEMATOLOGICAL TESTING SHOULD BE OBTAINED AS A BASELINE. IF A PATIENT IN THE COURSE OF TREATMENT EXHIBITS LOW OR DECREASED WHITE BLOOD CELL OR PLATELET COUNTS, THE PATIENT SHOULD BE MONITORED CLOSELY. DISCONTINUATION OF THE DRUG SHOULD BE CONSIDERED IF ANY EVIDENCE OF SIGNIFICANT BONE MARROW DEPRESSION DEVELOPS.

Before prescribing Carbatrol, the physician should be thoroughly familiar with the details of this prescribing information, particularly regarding use with other drugs, especially those which accentuate toxicity potential.

DESCRIPTION

CARBATROL is an anticonvulsant and specific analgesic for trigeminal neuralgia, available for oral administration as 100 mg, 200 mg and 300 mg extended-release capsules of Carbamazepine, USP. Carbamazepine is a white to off-white powder, practically insoluble in water and soluble in alcohol and in acetone. Its molecular weight is 236.27. Its chemical name is 5H-dibenz[b,f]azepine-5-carboxamide, and its structural formula is:

Carbatrol is a multi-component capsule formulation consisting of three different types of beads: immediate-release beads, extended-release beads, and enteric-release beads. The three bead types are combined in a specific ratio to provide twice daily dosing of Carbatrol.

Inactive ingredients: citric acid, colloidal silicon dioxide, lactose monohydrate, microcrystalline cellulose, polyethylene glycol, povidone, sodium lauryl sulfate, talc, triethyl citrate and other ingredients.

The 100 mg capsule shells contain gelatin-NF, FD&C Blue #2, Yellow Iron Oxide, and titanium dioxide and are imprinted with white ink; the 200 mg capsule shells contain gelatin-NF, FD&C Red #3, FD&C Yellow #6, Yellow Iron Oxide, FD&C Blue #2, and titanium dioxide, and are imprinted with white ink; and the 300 mg capsule shells contain gelatin-NF, FD&C Blue #2, FD&C Yellow #6, Red Iron Oxide, Yellow Iron Oxide, and titanium dioxide, and are imprinted with white ink.

CLINICAL PHARMACOLOGY

In controlled clinical trials, carbamazepine has been shown to be effective in the treatment of psychomotor and grand mal seizures, as well as trigeminal neuralgia.

Mechanism of Action

Carbamazepine has demonstrated anticonvulsant properties in rats and mice with electrically and chemically induced seizures. It appears to act by reducing polysynaptic responses and blocking the post-tetanic potentiation. Carbamazepine greatly reduces or abolishes pain induced by stimulation of the infraorbital nerve in cats and rats. It depresses thalamic potential and bulbar and polysynaptic reflexes, including the linguomandibular reflex in cats. Carbamazepine is chemically unrelated to other anticonvulsants or other drugs used to control the pain of trigeminal neuralgia. The mechanism of action remains unknown.

The principal metabolite of carbamazepine, carbamazepine-10,11-epoxide, has anticonvulsant activity as demonstrated in several in vivo animal models of seizures. Though clinical activity for the epoxide has been postulated, the significance of its activity with respect to the safety and efficacy of carbamazepine has not been established.

Pharmacokinetics

Carbamazepine (CBZ): Taken every 12 hours, carbamazepine extended-release capsules provide steady state plasma levels comparable to immediate-release carbamazepine tablets given every 6 hours, when administered at the same total mg daily dose.

Following a single 200 mg oral extended-release dose of carbamazepine, peak plasma concentration was 1.9 ± 0.3 μg/mL and the time to reach the peak was 19 ± 7 hours. Following chronic administration (800 mg every 12 hours), the peak levels were 11.0 ± 2.5 μg/mL and the time to reach the peak was 5.9 ± 1.8 hours. The pharmacokinetics of extended-release carbamazepine is linear over the single dose range of 200-800 mg.

Carbamazepine is 76% bound to plasma proteins. Carbamazepine is primarily metabolized in the liver. Cytochrome P450 3A4 was identified as the major isoform responsible for the formation of carbamazepine-10,11-epoxide. Since carbamazepine induces its own metabolism, the half-life is also variable. Following a single extended-release dose of carbamazepine, the average half-life range from 35-40 hours and 12-17 hours on repeated dosing. The apparent oral clearance following a single dose was 25 ± 5 mL/min and following multiple dosing was 80 ± 30 mL/min.

After oral administration of 14C-carbamazepine, 72% of the administered radioactivity was found in the urine and 28% in the feces. This urinary radioactivity was composed largely of hydroxylated and conjugated metabolites, with only 3% of unchanged carbamazepine.

Carbamazepine-10,11-epoxide (CBZ-E): Carbamazepine-10,11-epoxide is considered to be an active metabolite of carbamazepine. Following a single 200 mg oral extended-release dose of carbamazepine, the peak plasma concentration of carbamazepine-10,11-epoxide was 0.11 ± 0.012 μg/mL and the time to reach the peak was 36 ± 6 hours. Following chronic administration of an extended-release dose of carbamazepine (800 mg every 12 hours), the peak levels of carbamazepine-10,11-epoxide were 2.2 ± 0.9 μg/mL and the time to reach the peak was 14 ± 8 hours. The plasma half-life of carbamazepine-10,11-epoxide following administration of carbamazepine is 34 ± 9 hours. Following a single oral dose of extended-release carbamazepine (200-800 mg) the AUC and Cmax of carbamazepine-10,11-epoxide were less than 10% of carbamazepine. Following multiple dosing of extended-release carbamazepine (800-1600 mg daily for 14 days), the AUC and Cmax of carbamazepine-10,11-epoxide were dose related, ranging from 15.7 μg.hr/mL and 1.5 μg/mL at 800 mg/day to 32.6 μg.hr/mL and 3.2 μg/mL at 1600 mg/day, respectively, and were less than 30% of carbamazepine. Carbamazepine-10,11-epoxide is 50% bound to plasma proteins.

Food Effect: A high fat meal diet increased the rate of absorption of a single 400 mg dose (mean Tmax was reduced from 24 hours, in the fasting state, to 14 hours and Cmax increased from 3.2 to 4.3 μg/mL) but not the extent (AUC) of absorption. The elimination half-life remains unchanged between fed and fasting state. The multiple dose study conducted in the fed state showed that the steady-state Cmax values were within the therapeutic concentration range. The pharmacokinetic profile of extended-release carbamazepine was similar when given by sprinkling the beads over applesauce compared to the intact capsule administered in the fasted state.

Special Populations

Hepatic Dysfunction: The effect of hepatic impairment on the pharmacokinetics of carbamazepine is not known. However, given that carbamazepine is primarily metabolized in the liver, it is prudent to proceed with caution in patients with hepatic dysfunction.

Renal Dysfunction: The effect of renal impairment on the pharmacokinetics of carbamazepine is not known.

Gender: No difference in the mean AUC and Cmax of carbamazepine and carbamazepine-10,11-epoxide was found between males and females.

Age: Carbamazepine is more rapidly metabolized to carbamazepine-10,11-epoxide in young children than adults. In children below the age of 15, there is an inverse relationship between CBZ-E/CBZ ratio and increasing age.

Race: No information is available on the effect of race on the pharmacokinetics of carbamazepine.

INDICATIONS AND USAGE

Epilepsy

Carbatrol is indicated for use as an anticonvulsant drug. Evidence supporting efficacy of carbamazepine as an anticonvulsant was derived from active drug-controlled studies that enrolled patients with the following seizure types:

1. Partial seizures with complex symptomatology (psychomotor, temporal lobe). Patients with these seizures appear to show greater improvements than those with other types.
2. Generalized tonic-clonic seizures (grand mal).
3. Mixed seizure patterns which include the above, or other partial or generalized seizures. Absence seizures (petit mal) do not appear to be controlled by carbamazepine (see PRECAUTIONS, General).

Trigeminal Neuralgia

Carbatrol is indicated in the treatment of the pain associated with true trigeminal neuralgia. Beneficial results have also been reported in glossopharyngeal neuralgia. This drug is not a simple analgesic and should not be used for the relief of trivial aches or pains.

CONTRAINDICATIONS

Carbamazepine should not be used in patients with a history of previous bone marrow depression, hypersensitivity to the drug, or known sensitivity to any of the tricyclic compounds, such as amitriptyline, desipramine, imipramine, protriptyline and nortriptyline. Likewise, on theoretical grounds its use with monoamine oxidase inhibitors is not recommended. Before administration of carbamazepine, MAO inhibitors should be discontinued for a minimum of 14 days, or longer if the clinical situation permits.

Coadministration of carbamazepine and nefazodone may result in insufficient plasma concentrations of nefazodone and its active metabolite to achieve a therapeutic effect. Coadministration of carbamazepine with nefazodone is contraindicated.

Coadministration of Carbatrol is contraindicated with delavirdine due to the potential for loss of virologic response and possible resistance to delavirdine or to the class of non-nucleoside reverse transcriptase inhibitors.

WARNINGS

Serious Dermatologic Reactions

Serious and sometimes fatal dermatologic reactions, including toxic epidermal necrolysis (TEN) and Stevens-Johnson syndrome (SJS), have been reported with carbamazepine treatment. The risk of these events is estimated to be about 1 to 6 per 10,000 new users in countries with mainly Caucasian populations. However, the risk in some Asian countries is estimated to be about 10 times higher. Carbatrol should be discontinued at the first sign of a rash, unless the rash is clearly not drug-related. If signs or symptoms suggest SJS/TEN, use of this drug should not be resumed and alternative therapy should be considered.

SJS/TEN and HLA-B*1502 Allele

Retrospective case-control studies have found that in patients of Chinese ancestry there is a strong association between the risk of developing SJS/TEN with carbamazepine treatment and the presence of an inherited variant of the HLA-B gene, HLA-B*1502. The occurrence of higher rates of these reactions in countries with higher frequencies of this allele suggests that the risk may be increased in allele-positive individuals of any ethnicity.

Across Asian populations, notable variation exists in the prevalence of HLA-B*1502. Greater than 15% of the population is reported positive in Hong Kong, Thailand, Malaysia, and parts of the Philippines, compared to about 10% in Taiwan and 4% in North China. South Asians, including Indians, appear to have intermediate prevalence of HLA-B*1502, averaging 2 to 4%, but higher in some groups. HLA-B*1502 is present in <1% of the population in Japan and Korea.

HLA-B*1502 is largely absent in individuals not of Asian origin (e.g., Caucasians, African-Americans, Hispanics, and Native Americans).

Prior to initiating Carbatrol therapy, testing for HLA-B*1502 should be performed in patients with ancestry in populations in which HLA-B*1502 may be present. In deciding which patients to screen, the rates provided above for the prevalence of HLA-B*1502 may offer a rough guide, keeping in mind the limitations of these figures due to wide variability in rates even within ethnic groups, the difficulty in ascertaining ethnic ancestry, and the likelihood of mixed ancestry. Carbatrol should not be used in patients positive for HLA-B*1502 unless the benefits clearly outweigh the risks. Tested patients who are found to be negative for the allele are thought to have a low risk of SJS/TEN (see WARNINGS and PRECAUTIONS/Laboratory Tests).

Over 90% of carbamazepine treated patients who will experience SJS/TEN have this reaction within the first few months of treatment. This information may be taken into consideration in determining the need for screening of genetically at-risk patients currently on Carbatrol.

The HLA-B*1502 allele has not been found to predict risk of less severe adverse cutaneous reactions from carbamazepine, such as maculopapular eruption [MPE] or to predict Drug Reaction with Eosinophilia and Systemic Symptoms (DRESS).

Limited evidence suggests that HLA-B*1502 may be a risk factor for the development of SJS/TEN in patients of Chinese ancestry taking other anti-epileptic drugs associated with SJS/TEN, including phenytoin. Consideration should be given to avoiding use of other drugs associated with SJS/TEN in HLA-B*1502 positive patients, when alternative therapies are otherwise equally acceptable.

Patients should be made aware that Carbatrol contains carbamazepine and should not be used in combination with any other medications containing carbamazepine.

Hypersensitivity Reactions and HLA-A*3101 Allele

Retrospective case-control studies in patients of European, Korean, and Japanese ancestry have found a moderate association between the risk of developing hypersensitivity reactions and the presence of HLA-A*3101, an inherited allelic variant of the HLA-A gene, in patients using carbamazepine. These hypersensitivity reactions include SJS/TEN, maculopapular eruptions, and Drug Reaction with Eosinophilia and Systemic Symptoms (see DRESS/Multiorgan hypersensitivity below).

HLA-A*3101 is expected to be carried by more than 15% of patients of Japanese, Native American, Southern Indian (e.g., Tamil Nadu) and some Arabic ancestry; up to about 10% in patients of Han Chinese, Korean, European, Latin American and other Indian ancestry; and up to about 5% in African-Americans and patients of Thai, Taiwanese, and Chinese (Hong Kong) ancestry.

The risks and benefits of carbamazepine therapy should be weighed before considering carbamazepine in patients known to be positive for HLA-A*3101.

General Information on HLA Genotyping and Hypersensitivity

Application of HLA genotyping as a screening tool has important limitations and must never substitute for appropriate clinical vigilance and patient management. Many HLA-B*1502-positive and HLA-A*3101-positive patients treated with carbamazepine will not develop SJS/TEN or other hypersensitivity reactions, and these reactions can still occur infrequently in HLA-B*1502-negative and HLA-A*3101-negative patients of any ethnicity. The role of other possible factors in the development of, and morbidity from, SJS/TEN and other hypersensitivity reactions, such as AED dose, compliance, concomitant medications, co-morbidities, and the level of dermatologic monitoring have not been studied.

Aplastic anemia and agranulocytosis have been reported in association with the use of carbamazepine. (See BOXED WARNING.) Patients with a history of adverse hematologic reaction to any drug may be particularly at risk of bone marrow depression.

Drug Reaction with Eosinophilia and Systemic Symptoms (DRESS)/Multiorgan Hypersensitivity

Drug Reaction with Eosinophilia and Systemic Symptoms (DRESS), also known as multiorgan hypersensitivity, have occurred with carbamazepine. Some of these events have been fatal or life-threatening. DRESS typically, although not exclusively, presents with fever, rash, lymphadenopathy and/or facial swelling in association with other organ system involvement, such as hepatitis, nephritis, hematologic abnormalities, myocarditis, or myositis sometimes resembling an acute viral infection. Eosinophilia is often present. This disorder is variable in its expression, and other organ systems not noted here may be involved. It is important to note that early manifestations of hypersensitivity (e.g., fever, lymphadenopathy) may be present even though rash is not evident. If such signs or symptoms are present, the patient should be evaluated immediately. Carbatrol should be discontinued if an alternative etiology for the signs or symptoms cannot be established.

Hypersensitivity

Hypersensitivity reactions to carbamazepine have been reported in patients who previously experienced this reaction to anticonvulsants including phenytoin, primidone, and phenobarbital. A history of hypersensitivity reactions should be obtained for patients and their immediate family members. If such history is present, benefits and risks should be carefully considered, and, if carbamazepine is initiated, the signs and symptoms of hypersensitivity should be carefully monitored.

In patients who have exhibited hypersensitivity reactions to carbamazepine, approximately 25 to 30% may experience hypersensitivity reactions with oxcarbazepine (Trileptal®).

Anaphylaxis and Angioedema

Rare cases of anaphylaxis and angioedema involving the larynx, glottis, lips, and eyelids have been reported in patients after taking the first or subsequent doses of carbamazepine. Angioedema associated with laryngeal edema can be fatal. If a patient develops any of these reactions after treatment with Carbatrol, the drug should be discontinued and an alternative treatment started. These patients should not be rechallenged with the drug.

Withdrawal Precipitated Seizure, Status Epilepticus

Antiepileptic drugs should not be abruptly discontinued because of the possibility of increased seizure frequency, including status epilepticus. When in the judgment of the clinician, the need for dosage reduction, discontinuation, or substitution of alternative anticonvulsant medication arises, this should be done gradually. However, in the event of an allergic or hypersensitivity reaction, more rapid substitution of alternative therapy may be necessary.

Suicidal Behavior and Ideation

Antiepileptic drugs (AEDs), including Carbatrol, increase the risk of suicidal thoughts or behavior in patients taking these drugs for any indication. Patients treated with any AED for any indication should be monitored for the emergence or worsening of depression, suicidal thoughts or behavior, and/or any unusual changes in mood or behavior.

Pooled analyses of 199 placebo-controlled clinical trials (mono- and adjunctive therapy) of 11 different AEDs showed that patients randomized to one of the AEDs had approximately twice the risk (adjusted Relative Risk 1.8, 95% CI:1.2, 2.7) of suicidal thinking or behavior compared to patients randomized to placebo. In these trials, which had a median treatment duration of 12 weeks, the estimated incidence rate of suicidal behavior or ideation among 27,863 AED-treated patients was 0.43%, compared to 0.24% among 16,029 placebo-treated patients, representing an increase of approximately one case of suicidal thinking or behavior for every 530 patients treated. There were four suicides in drug-treated patients in the trials and none in placebo-treated patients, but the number is too small to allow any conclusion about drug effect on suicide.

The increased risk of suicidal thoughts or behavior with AEDs was observed as early as one week after starting drug treatment with AEDs and persisted for the duration of treatment assessed. Because most trials included in the analysis did not extend beyond 24 weeks, the risk of suicidal thoughts or behavior beyond 24 weeks could not be assessed.

The risk of suicidal thoughts or behavior was generally consistent among drugs in the data analyzed. The finding of increased risk with AEDs of varying mechanisms of action and across a range of indications suggests that the risk applies to all AEDs used for any indication. The risk did not vary substantially by age (5-100 years) in the clinical trials analyzed.

Table 1 shows absolute and relative risk by indication for all evaluated AEDs.

Table 1 – Risk by Indication for Antiepileptic Drugs in the Pooled Analysis
Indication | Placebo Patients with Events Per 1000 Patients | Drug Patients with Events Per 1000 Patients | Relative Risk: Incidence of Events in Drug Patients/ Incidence in Placebo Patients | Risk Difference:; Additional Drug Patients with Events Per 1000 Patients
Epilepsy | 1.0 | 3.4 | 3.5 | 2.4
Psychiatric | 5.7 | 8.5 | 1.5 | 2.9
Other | 1.0 | 1.8 | 1.9 | 0.9
Total | 2.4 | 4.3 | 1.8 | 1.9

The relative risk for suicidal thoughts or behavior was higher in clinical trials for epilepsy than in clinical trials for psychiatric or other conditions, but the absolute risk differences were similar for the epilepsy and psychiatric indications.

Anyone considering prescribing Carbatrol or any other AED must balance the risk of suicidal thoughts or behavior with the risk of untreated illness. Epilepsy and many other illnesses for which AEDs are prescribed are themselves associated with morbidity and mortality and an increased risk of suicidal thoughts or behavior. Should suicidal thoughts and behavior emerge during treatment, the prescriber needs to consider whether the emergence of these symptoms in any given patient may be related to the illness being treated.

Hyponatremia, Syndrome of Inappropriate Antidiuretic Hormone Secretion, and Water Intoxication

Hyponatremia can occur as a result of treatment with Carbatrol. In many cases, this hyponatremia appears to be the result of the syndrome of inappropriate antidiuretic hormone secretion (SIADH). The risk of developing SIADH with Carbatrol treatment may be dose-related. Elderly patients and patients treated with diuretics are at greater risk of developing hyponatremia. Signs and symptoms of hyponatremia include headache, new or increased seizure frequency, difficulty concentrating, memory impairment, confusion, weakness, and unsteadiness, which can lead to falls. Consider discontinuing Carbatrol in patients with symptomatic hyponatremia.

Usage in Pregnancy

Carbamazepine can cause fetal harm when administered to a pregnant woman.

Epidemiological data suggest that there may be an association between the use of carbamazepine during pregnancy and congenital malformations, including spina bifida. There have also been reports that associate carbamazepine with developmental disorders and congenital anomalies (e.g., craniofacial defects, cardiovascular malformations, and anomalies involving various body systems). Developmental delays have been reported. When treating or counseling women of childbearing potential, the prescribing physician will wish to weigh the benefits of therapy against the risks. If this drug is used during pregnancy, or if the patient becomes pregnant while taking this drug, the patient should be apprised of the potential hazard to the fetus.

Retrospective case reviews suggest that, compared with monotherapy, there may be a higher prevalence of teratogenic effects associated with the use of anticonvulsants in combination therapy. Therefore, if therapy is to be continued, monotherapy may be preferable for pregnant women.

In humans, transplacental passage of carbamazepine is rapid (30-60 minutes), and the drug is accumulated in the fetal tissues, with higher levels found in liver and kidney than in brain and lung.

Carbamazepine has been shown to have adverse effects in reproduction studies in rats when given orally in dosages 10-25 times the maximum human daily dosage (MHDD) of 1200 mg on a mg/kg basis or 1.5-4 times the MHDD on a mg/m^2 basis. In rat teratology studies, 2 of 135 offspring showed kinked ribs at 250 mg/kg and 4 of 119 offspring at 650 mg/kg showed other anomalies (cleft palate, 1; talipes, 1; anophthalmos, 2). In reproduction studies in rats, nursing offspring demonstrated a lack of weight gain and an unkempt appearance at a maternal dosage level of 200 mg/kg.

Antiepileptic drugs should not be discontinued abruptly in patients in whom the drug is administered to prevent major seizures because of the strong possibility of precipitating status epilepticus with attendant hypoxia and threat to life. In individual cases where the severity and frequency of the seizure disorder are such that removal of medication does not pose a serious threat to the patient, discontinuation of the drug may be considered prior to and during pregnancy, although it cannot be said with any confidence that even minor seizures do not pose some hazard to the developing embryo or fetus.

Tests to detect defects using current accepted procedures should be considered a part of routine prenatal care in childbearing women receiving carbamazepine.

There have been a few cases of neonatal seizures and/or respiratory depression reported in association with maternal carbamazepine and other concomitant anticonvulsant drug use. A few cases of neonatal vomiting, diarrhea, and/or decreased feeding have also been reported in association with maternal carbamazepine use. These symptoms may represent a neonatal withdrawal syndrome.

To provide information regarding the effects of in utero exposure to Carbatrol, physicians are advised to recommend that pregnant patients taking Carbatrol enroll in the North American Antiepileptic Drug (NAAED) Pregnancy Registry. This can be done by calling the toll free number 1-888-233-2334, and must be done by patients themselves. Information on the registry can also be found at the website http://www.aedpregnancyregistry.org/.

General

Carbamazepine has shown mild anticholinergic activity; therefore, patients with increased intraocular pressure should be closely observed during therapy.

Because of the relationship of the drug to other tricyclic compounds, the possibility of activation of a latent psychosis and, in elderly patients, of confusion or agitation should be considered.

The use of Carbatrol should be avoided in patients with a history of hepatic porphyria (e.g., acute intermittent porphyria, variegate porphyria, porphyria cutanea tarda). Acute attacks have been reported in such patients receiving Carbatrol therapy. Carbamazepine administration has also been demonstrated to increase porphyrin precursors in rodents, a presumed mechanism for the induction of acute attacks of porphyria.

PRECAUTIONS

General

Before initiating therapy, a detailed history and physical examination should be made.

Carbatrol should be used with caution in patients with a mixed seizure disorder that includes atypical absence seizures, since in these patients carbamazepine has been associated with increased frequency of generalized convulsions (see INDICATIONS AND USAGE).

Therapy should be prescribed only after critical benefit-to-risk appraisal in patients with a history of cardiac conduction disturbance, including second- and third-degree atrioventricular (AV) block; cardiac, hepatic, or renal damage; adverse hematologic or hypersensitivity reaction to other drugs including reactions to other anticonvulsants; or interrupted courses of therapy with carbamazepine.

AV block, including second- and third-degree block, has been reported following carbamazepine treatment. This occurred generally, but not solely, in patients with underlying EKG abnormalities or risk factors for conduction disturbances.

Hepatic effects, ranging from slight elevations in liver enzymes to rare cases of hepatic failure, have been reported (see ADVERSE REACTIONS and PRECAUTIONS, Laboratory Tests). In some cases, hepatic effects may progress despite discontinuation of the drug. In addition, rare instances of vanishing bile duct syndrome have been reported. This syndrome consists of a cholestatic process with a variable clinical course ranging from fulminant to indolent, involving the destruction and disappearance of the intrahepatic bile ducts. Some, but not all, cases are associated with features that overlap with other immunoallergenic syndromes such as multiorgan hypersensitivity/ DRESS and serious dermatologic reactions. As an example, there has been a report of vanishing bile duct syndrome associated with Stevens-Johnson syndrome and in another case an association with fever and eosinophilia.

Information for Patients

Patients should be informed of the availability of a Medication Guide and they should be instructed to read the Medication Guide before taking Carbatrol.

Patients should be made aware of the early toxic signs and symptoms of potential hematologic, dermatologic, hypersensitivity, or hepatic reactions. These symptoms may include, but are not limited to, fever, sore throat, rash, ulcers in the mouth, easy bruising, lymphadenopathy and petechial or purpuric hemorrhage, and in the case of liver reactions, anorexia, nausea/vomiting, or jaundice. Patients should be advised that, because these signs and symptoms may signal a serious reaction, they must report any occurrence immediately to their physicians. In addition, the patient should be advised that these signs and symptoms should be reported even if mild or when occurring after extended use.

Patients should be advised that serious skin reactions have been reported in association with Carbatrol. In the event a skin reaction should occur while taking Carbatrol, patients should consult with their physician immediately (see WARNINGS).

Patients should be advised that anaphylactic reactions and angioedema may occur during treatment with Carbatrol (see WARNINGS). Advise patients to immediately report signs and symptoms suggesting angioedema (swelling of the face, eyes, lips, or tongue, or difficulty in swallowing or breathing) and to stop taking the drug until they have consulted with their healthcare provider.

Patients, their caregivers, and families should be counseled that AEDs, including Carbatrol, may increase the risk of suicidal thoughts and behavior and should be advised of the need to be alert for the emergence or worsening of symptoms of depression, any unusual changes in mood or behavior, or the emergence of suicidal thoughts, behavior, or thoughts about self-harm. Behaviors of concern should be reported immediately to healthcare providers.

Carbatrol may interact with some drugs. Therefore, patients should be advised to report to their doctors the use of any other prescription or nonprescription medications or herbal products.

Caution should be exercised if alcohol is taken in combination with Carbatrol therapy, due to a possible additive sedative effect.

Since dizziness and drowsiness may occur, patients should be cautioned about the hazards of operating machinery or automobiles or engaging in other potentially dangerous tasks.

Patients should be encouraged to enroll in the NAAED Pregnancy Registry if they become pregnant. This registry is collecting information about the safety of antiepileptic drugs during pregnancy. To enroll, patients can call the toll-free number 1-888-233-2334 (see Warnings - Usage in Pregnancy).

If necessary, the Carbatrol capsules can be opened and the contents sprinkled over food, such as a teaspoon of applesauce or other similar food products. Carbatrol capsules or their contents should not be crushed or chewed.

Carbatrol may interact with some drugs. Therefore, patients should be advised to report to their doctors the use of any other prescription or non-prescription medication or herbal products.

Patients, their caregivers, and families should be informed of the availability of a Medication Guide, and they should be instructed to read the Medication Guide prior to taking Carbatrol. See FDA approved Medication Guide.

Laboratory Tests

For genetically at-risk patients (see WARNINGS), high-resolution 'HLA-B*1502 typing' is recommended. The test is positive if either one or two HLA-B*1502 alleles are detected and negative if no HLA-B*1502 alleles are detected.

Complete pretreatment blood counts, including platelets and possibly reticulocytes and serum iron, should be obtained as a baseline. If a patient in the course of treatment exhibits low or decreased white blood cell or platelet counts, the patient should be monitored closely. Discontinuation of the drug should be considered if any evidence of significant bone marrow depression develops.

Baseline and periodic evaluations of liver function, particularly in patients with a history of liver disease, must be performed during treatment with this drug since liver damage may occur (see PRECAUTIONS, General and ADVERSE REACTIONS, Liver). Carbatrol should be discontinued based on clinical judgement, if indicated by newly occurring or worsening clinical or laboratory evidence of liver dysfunction or hepatic damage, or in the case of active liver disease.

Baseline and periodic eye examinations, including slit-lamp, funduscopy, and tonometry, are recommended since many phenothiazines and related drugs have been shown to cause eye changes.

Baseline and periodic complete urinalysis and BUN determinations are recommended for patients treated with this agent because of observed renal dysfunction.

Increases in total cholesterol, LDL and HDL have been observed in some patients taking anticonvulsants. Therefore, periodic evaluation of these parameters is also recommended.

Monitoring of blood levels (see CLINICAL PHARMACOLOGY) has increased the efficacy and safety of anticonvulsants. This monitoring may be particularly useful in cases of dramatic increase in seizure frequency and for verification of compliance. In addition, measurement of drug serum levels may aid in determining the cause of toxicity when more than one medication is being used.

Thyroid function tests have been reported to show decreased values with carbamazepine administered alone.

Interference with some pregnancy tests has been reported.

Drug Interactions

Clinically meaningful drug interactions have occurred with concomitant medications and include, but are not limited to the following:

Agents Highly Bound to Plasma Protein:

Carbamazepine is not highly bound to plasma proteins; therefore, administration of Carbatrol to a patient taking another drug that is highly protein bound should not cause increased free concentrations of the other drug.

Agents that Inhibit Cytochrome P450 Isoenzymes and/or Epoxide Hydrolase:

Carbamazepine is metabolized mainly by cytochrome P450 (CYP) 3A4 to the active carbamazepine 10,11-epoxide, which is further metabolized to the trans-diol by epoxide hydrolase. Therefore, the potential exists for interaction between carbamazepine and any agent that inhibits CYP3A4 and/or epoxide hydrolase. Agents that are CYP3A4 inhibitors that have been found, or are expected, to increase plasma levels of Carbatrol include, for example, the following:

Acetazolamide, aprepitant, azole antifungals (e.g., ketoconazole, itraconazole, fluconazole, voriconazole), cimetidine, ciprofloxacin, clarithromycin, dalfopristin, danazol, dantrolene, delavirdine, diltiazem, erythromycin, fluoxetine, fluvoxamine, grapefruit juice, ibuprofen, isoniazid, loratadine, macrolides, nefazodone, niacinamide, nicotinamide, olanzapine, omeprazole, oxybutynin, protease inhibitors, propoxyphene, quinine, quinupristin, ticlopidine, troleandomycin, valproate, verapamil, zileuton.

Human microsomal epoxide hydrolase has been identified as the enzyme responsible for the formation of the 10,11-transdiol derivative from carbamazepine-10,11 epoxide. Coadministration of inhibitors of human microsomal epoxide hydrolase may result in increased carbamazepine-10,11 epoxide plasma concentrations. Accordingly, the dosage of Carbatrol should be adjusted and/or the plasma levels monitored when used concomitantly with loxapine, quetiapine, or valproic acid.

Thus, if a patient has been titrated to a stable dosage of Carbatrol, and then begins a course of treatment with one of these CYP3A4 or epoxide hydrolase inhibitors, it is reasonable to expect that a dose reduction for Carbatrol may be necessary.

Agents that Induce Cytochrome P450 Isoenzymes:

Carbamazepine is metabolized by CYP3A4. Therefore, the potential exists for interaction between carbamazepine and any agent that induces CYP3A4. Agents that are CYP inducers that have been found, or are expected, to decrease plasma levels of Carbatrol include, for example, the following:

Aminophylline, cisplatin, doxorubicin HCL, felbamate, fosphenytoin, methsuximide, phenobarbital, phenytoin(^1), primidone, rifampin and theophylline.

(1)Phenytoin plasma levels have also been reported to increase and decrease in the presence of carbamazepine, see below.

Thus, if a patient has been titrated to a stable dosage on Carbatrol, and then begins a course of treatment with one of these CYP3A4 inducers, it is reasonable to expect that a dose increase for Carbatrol may be necessary.

Agents with Decreased Levels in the Presence of Carbamazepine due to Induction of Cytochrome P450 Enzymes:

Carbamazepine is a potent inducer of hepatic CYP3A4 and is also known to be an inducer of CYP1A2, 2B6, 2C9/19 and may therefore reduce plasma concentrations of co-medications mainly metabolized by CYP 1A2, 2B6, 2C9/19 and 3A4, through induction of their metabolism. When used concomitantly with Carbatrol, monitoring of concentrations or dosage adjustment of these agents may be necessary:

- When carbamazepine is added to aripiprazole, the aripiprazole dose should be doubled. Additional dose increases should be based on clinical evaluation. If carbamazepine is later withdrawn, the aripiprazole dose should be reduced.
- When carbamazepine is used with tacrolimus, monitoring of tacrolimus blood concentrations and appropriate dosage adjustments are recommended.
- The use of concomitant strong CYP3A4 inducers such as carbamazepine should be avoided with temsirolimus. If patients must be coadministered carbamazepine with temsirolimus, an adjustment of temsirolimus dosage should be considered.
- The use of carbamazepine with lapatinib should generally be avoided. If carbamazepine is started in a patient already taking lapatinib, the dose of lapatinib should be gradually titrated up. If carbamazepine is discontinued, the lapatinib dose should be reduced.
- Concomitant use of carbamazepine with nefazodone results in plasma concentrations of nefazodone and its active metabolite insufficient to achieve a therapeutic effect. Coadministration of carbamazepine with nefazodone is contraindicated (see CONTRAINDICATIONS).
- Monitor concentrations of valproate when Carbatrol is introduced or withdrawn in patients using valproic acid.

In addition, Carbatrol causes, or would be expected to cause, decreased levels of, for example, the following drugs, for which monitoring of concentrations or dosage adjustment may be necessary:

Acetaminophen, albendazole, alprazolam, aprepitant, buprenorphine, apixaban(^6), bupropion, buspirone, citalopram, clobazam, clonazepam, clozapine, corticosteroids (e.g. prednisolone, dexamethasone), cyclosporin, dabigatran(^6), delavirdine, desipramine, diazepam, dicumarol, dihydropyridine calcium channel blockers (e.g., felodipine), doxycycline, edoxaban(^6), eslicarbazepine, ethosuximide, everolimus, felbamate, haloperidol, imatinib, itraconazole, lamotrigine, levothyroxine, lorazepam, methadone, methsuximide, midazolam, mirtazapine, nefazodone, nortriptyline, olanzapine, oral and other hormonal contraceptives(^2), oxcarbazepine, paliperidone, phenytoin(^3), praziquantel, protease inhibitors, quetiapine, risperidone, rivaroxaban(^6), sertraline, sirolimus, tadalafil, theophylline, tiagabine, topiramate, tramadol, triazolam, trazodone(^4), tricyclic antidepressants (e.g., imipramine, amitriptyline, nortriptyline), valproate, warfarin (^5), ziprasidone, and zonisamide.

(2)Concomitant use of Carbatrol with hormonal contraceptive products (e.g., oral and levonorgestrel subdermal implant contraceptives) may render the contraceptives less effective because the plasma concentrations of the hormones may be decreased. Breakthrough bleeding and unintended pregnancies have been reported with carbamazepine. Alternative or back-up methods of contraception should be considered.

(3)Phenytoin has also been reported to increase in the presence of carbamazepine. Careful monitoring of phenytoin plasma levels following co-medication with carbamazepine is advised.

(4)Following co-administration of carbamazepine 400mg/day with trazodone 100mg to 300mg daily, carbamazepine reduced trough plasma concentrations of trazodone (as well as meta-chlorophenylpiperazine [mCPP]) by 76 and 60% respectively, compared to precarbamazepine values.

(5)Warfarin's anticoagulant effect can be reduced in the presence of carbamazepine.

(6)Concomitant use of carbamazepine with rivaroxaban, apixaban, dabigatran, and edoxaban (direct acting oral anticoagulants) is expected to result in decreased plasma concentrations of these anticoagulants that may be insufficient to achieve the intended therapeutic effect. In general, coadministration of carbamazepine with rivaroxaban, apixaban, dabigatran, and edoxaban should be avoided.

Thus, if a patient has been titrated to a stable dosage on one of the agents in this category, and then begins a course of treatment with Carbatrol, it is reasonable to expect that a dose increase for the concomitant agent may be necessary.

Agents with Increased Levels in the Presence of Carbamazepine:

Carbatrol increases the plasma levels of the following agents. Thus, if a patient has been titrated to a stable dosage on one of the agents in this category, and then begins a course of the treatment with Carbatrol, it is reasonable to expect that a dose decrease for the concomitant agent may be necessary.

Clomipramine HCl, Phenytoin(^7), and Primidone

Carbatrol can increase the concentrations of clomipramine, phenytoin, and primidone. If a patient has been titrated to a stable dosage on one of these agents in this category, and then begins treatment with Carbatrol, it may be necessary to decrease the dose of these drugs.

(7)Phenytoin has also been reported to decrease in the presence of carbamazepine. Careful monitoring of phenytoin plasma levels following co-medication with carbamazepine is advised.

Cyclophosphamide

Cyclophosphamide is an inactive prodrug and is converted to its active metabolite in part by CYP3A. The rate of metabolism and the leukopenic activity of cyclophosphamide are reportedly increased by chronic co-administration of CYP3A4 inducers. There is a potential for increased cyclophosphamide toxicity when coadministered with carbamazepine.

Pharmacological/Pharmacodynamic Interactions with Carbamazepine:

Delavirdine

Coadministration of Carbatrol with delavirdine may lead to loss of virologic response and possible resistance to delavirdine or to the class of non-nucleoside reverse transcriptase inhibitors (see CONTRAINDICATIONS).

Lithium

Concomitant administration of carbamazepine and lithium may increase the risk of neurotoxic side effects.

Thyroid Effects with Other Anticonvulsant Medications

Alterations of thyroid function have been reported in combination therapy with other anticonvulsant medications.

Chloroquine and Mefloquine

Anti-malarial drugs, such as chloroquine and mefloquine, may antagonize the activity of carbamazepine.

Thus if a patient has been titrated to a stable dosage on one of the agents in this category, and then begins a course of treatment with Carbatrol, it is reasonable to expect that a dose adjustment may be necessary.

CNS Depressants

The concomitant use of Carbatrol and other CNS depressants can increase the risk of respiratory depression, profound sedation, hypotension, and syncope. CNS depressants include: alcohol, opioid analgesics, benzodiazepines, tricyclic antidepressants, sedative/hypnotics, anticonvulsants, antipsychotics, antihistamines, anticholinergics, alpha and beta blockers, general anesthetics, muscle relaxants, and illicit CNS depressants. Consider reducing the dose of CNS depressants or Carbatrol when using these drugs concomitantly. Because of its primary CNS effect, caution should be used when Carbatrol is taken with other centrally acting drugs and alcohol.

Neuromuscular Blocking Agents

Resistance to the neuromuscular blocking action of the nondepolarizing neuromuscular blocking agents pancuronium, vecuronium, rocuronium and cisatracurium has occurred in patients chronically administered carbamazepine. Whether or not carbamazepine has the same effect on other nondepolarizing agents is unknown. Patients should be monitored closely for more rapid recovery from neuromuscular blockade than expected, and infusion rate requirements may be higher.

Carcinogenesis, Mutagenesis, Impairment of Fertility:

Administration of carbamazepine to Sprague-Dawley rats for two years in the diet at doses of 25, 75, and 250 mg/kg/day (low dose approximately 0.2 times the maximum human daily dose of 1200 mg on a mg/m^2 basis), resulted in a dose-related increase in the incidence of hepatocellular tumors in females and of benign interstitial cell adenomas in the testes of males.

Carbamazepine must, therefore, be considered to be carcinogenic in Sprague-Dawley rats. Bacterial and mammalian mutagenicity studies using carbamazepine produced negative results. The significance of these findings relative to the use of carbamazepine in humans is, at present, unknown.

Usage in Pregnancy

(See WARNINGS)

Labor and Delivery

The effect of carbamazepine on human labor and delivery is unknown.

Nursing Mothers

Carbamazepine and its epoxide metabolite are transferred to breast milk and during lactation. The concentrations of carbamazepine and its epoxide metabolite are approximately 50% of the maternal plasma concentration. Because of the potential for serious adverse reactions in nursing infants from carbamazepine, a decision should be made whether to discontinue nursing or to discontinue the drug, taking into account the importance of the drug to the mother.

Pediatric Use

Substantial evidence of carbamazepine effectiveness for use in the management of children with epilepsy (see INDICATIONS for specific seizure types) is derived from clinical investigations performed in adults and from studies in several in vitro systems which support the conclusion that (1) the pathogenic mechanisms underlying seizure propagation are essentially identical in adults and children, and (2) the mechanism of action of carbamazepine in treating seizures is essentially identical in adults and children.

Taken as a whole, this information supports a conclusion that the generally acceptable therapeutic range of total carbamazepine in plasma (i.e., 4-12 μg/mL) is the same in children and adults.

The evidence assembled was primarily obtained from short-term use of carbamazepine. The safety of carbamazepine in children has been systematically studied up to 6 months. No longer term data from clinical trials is available.

Geriatric Use

No systematic studies in geriatric patients have been conducted.

ADVERSE REACTIONS

General: If adverse reactions are of such severity that the drug must be discontinued, the physician must be aware that abrupt discontinuation of any anticonvulsant drug in a responsive patient with epilepsy may lead to seizures or even status epilepticus with its life-threatening hazards.

The most severe adverse reactions previously observed with carbamazepine were reported in the hemopoietic system and skin (see BOXED WARNING), and the cardiovascular system.

The most frequently observed adverse reactions, particularly during the initial phases of therapy, are dizziness, drowsiness, unsteadiness, nausea, and vomiting. To minimize the possibility of such reactions, therapy should be initiated at the lowest dosage recommended.

The following additional adverse reactions were previously reported with carbamazepine:

Hemopoietic System: Aplastic anemia, agranulocytosis, pancytopenia, bone marrow depression, thrombocytopenia, leukopenia, leukocytosis, eosinophilia, acute intermittent porphyria.

Skin: Toxic epidermal necrolysis (TEN) and Stevens-Johnson syndrome (SJS) (see BOXED WARNING), Acute Generalized Exanthematous Pustulosis (AGEP), pruritic and erythematous rashes, urticaria, photosensitivity reactions, alterations in skin pigmentation, exfoliative dermatitis, erythema multiforme and nodosum, purpura, aggravation of disseminated lupus erythematosus, alopecia, diaphoresis, onychomadesis and hirsutism. In certain cases, discontinuation of therapy may be necessary.

Cardiovascular System: Congestive heart failure, edema, aggravation of hypertension, hypotension, syncope and collapse, aggravation of coronary artery disease, arrhythmias and AV block, thrombophlebitis, thromboembolism, and adenopathy or lymphadenopathy. Some of these cardiovascular complications have resulted in fatalities. Myocardial infarction has been associated with other tricyclic compounds.

Immune system disorders: Hypogammaglobulinemia.

Liver: Abnormalities in liver function tests, cholestatic and hepatocellular jaundice, hepatitis, and hepatic failure.

Pancreatic: Pancreatitis.

Respiratory System: Pulmonary hypersensitivity characterized by fever, dyspnea, pneumonitis, or pneumonia.

Genitourinary System: Urinary frequency, acute urinary retention, oliguria with elevated blood pressure, azotemia, renal failure, and impotence. Albuminuria, glycosuria, elevated BUN, and microscopic deposits in the urine have also been reported. There have been rare reports of impaired male fertility and/or abnormal spermatogenesis.

Testicular atrophy occurred in rats receiving carbamazepine orally from 4-52 weeks at dosage levels of 50-400 mg/kg/day. Additionally, rats receiving carbamazepine in the diet for 2 years at dosage levels of 25, 75, and 250 mg/kg/day had a dose-related incidence of testicular atrophy and aspermatogenesis. In dogs, it produced a brownish discoloration, presumably a metabolite, in the urinary bladder at dosage levels of 50 mg/kg/day and higher. Relevance of these findings to humans is unknown.

Nervous System: Dizziness, drowsiness, disturbances of coordination, confusion, headache, fatigue, blurred vision, visual hallucinations, transient diplopia, oculomotor disturbances, nystagmus, speech disturbances, abnormal involuntary movements, peripheral neuritis and paresthesias, depression with agitation, talkativeness, tinnitus, and hyperacusis.

There have been reports of associated paralysis and other symptoms of cerebral arterial insufficiency, but the exact relationship of these reactions to the drug has not been established.

Isolated cases of neuroleptic malignant syndrome have been reported with concomitant use of psychotropic drugs.

Digestive System: Nausea, vomiting, gastric distress and abdominal pain, diarrhea, constipation, anorexia, and dryness of the mouth and pharynx, including glossitis and stomatitis.

Eyes: Scattered punctate cortical lens opacities, as well as conjunctivitis, have been reported. Although a direct causal relationship has not been established, many phenothiazines and related drugs have been shown to cause eye changes.

Musculoskeletal System: Bone loss, aching joints and muscles, and leg cramps.

Metabolism: Fever and chills, decreased levels of plasma calcium leading to osteoporosis, and hyperammonemia have been reported.

Other: Isolated cases of a lupus erythematosus-like syndrome have been reported. There have been occasional reports of elevated levels of cholesterol, HDL cholesterol, and triglycerides in patients taking anticonvulsants.

A case of aseptic meningitis, accompanied by myoclonus and peripheral eosinophilia, has been reported in a patient taking carbamazepine in combination with other medications. The patient was successfully dechallenged, and the meningitis reappeared upon rechallenge with carbamazepine.

DRUG ABUSE AND DEPENDENCE

No evidence of abuse potential has been associated with carbamazepine, nor is there evidence of psychological or physical dependence in humans.

OVERDOSAGE

Acute Toxicity

Lowest known lethal dose: adults, >60 g (39-year-old man). Highest known doses survived: adults, 30 g (31-year-old woman); children, 10 g (6-year-old boy); small children, 5 g (3-year-old girl).

Oral LD50 in animals (mg/kg): mice, 1100-3750; rats, 3850-4025; rabbits, 1500-2680; guinea pigs, 920.

Signs and Symptoms

The first signs and symptoms appear after 1-3 hours. Neuromuscular disturbances are the most prominent. Cardiovascular disorders are generally milder, and severe cardiac complications occur only when very high doses (>60 g) have been ingested.

Respiration: Irregular breathing, respiratory depression.

Cardiovascular System: Tachycardia, hypotension or hypertension, shock, conduction disorders.

Nervous System and Muscles: Impairment of consciousness ranging in severity to deep coma. Convulsions, especially in small children. Motor restlessness, muscular twitching, tremor, athetoid movements, opisthotonos, ataxia, drowsiness, dizziness, mydriasis, nystagmus, adiadochokinesia, ballism, psychomotor disturbances, dysmetria. Initial hyperreflexia, followed by hyporeflexia.

Gastrointestinal Tract: Nausea, vomiting.

Kidneys and Bladder: Anuria or oliguria, urinary retention.

Laboratory Findings: Isolated instances of overdosage have included leukocytosis, reduced leukocyte count, glycosuria, and acetonuria. ECG may show dysrhythmias.

Combined Poisoning: When alcohol, tricyclic antidepressants, barbiturates, or hydantoins are taken at the same time, the signs and symptoms of acute poisoning with carbamazepine may be aggravated or modified.

Treatment

For the most up to date information on management of carbamazepine overdose, please contact the poison center for your area by calling 1-800-222-1222. The prognosis in cases of carbamazepine poisoning is generally favorable. Of 5,645 cases of carbamazepine exposures reported to US poison centers in 2002, a total of 8 deaths (0.14% mortality rate) occurred. Over 39% of the cases reported to these poison centers were managed safely at home with conservative care. Successful management of large or intentional carbamazepine exposures requires implementation of supportive care, frequent monitoring of serum drug concentrations, as well as aggressive but appropriate gastric decontamination.

Elimination of the Drug: The primary method for gastric decontamination of carbamazepine overdose is use of activated charcoal. For substantial recent ingestions, gastric lavage may also be considered. Administration of activated charcoal prior to hospital assessment has the potential to significantly reduce drug absorption. There is no specific antidote. In overdose, absorption of carbamazepine may be prolonged and delayed. More than one dose of activated charcoal may be beneficial in patients that have evidence of continued absorption (e.g., rising serum carbamazepine levels).

Measures to Accelerate Elimination: The data on use of dialysis to enhance elimination in carbamazepine is scarce. Dialysis, particularly high flux or high efficiency hemodialysis, may be considered in patients with severe carbamazepine poisoning associated with renal failure or in cases of status epilepticus, or where there are rising serum drug levels and worsening clinical status despite appropriate supportive care and gastric decontamination. For severe cases of carbamazepine overdose unresponsive to other measures, charcoal hemoperfusion may be used to enhance drug clearance.

Respiratory Depression: Keep the airways free; resort, if necessary, to endotracheal intubation, artificial respiration, and administration of oxygen.

Hypotension, Shock: Keep the patient's legs raised and administer a plasma expander. If blood pressure fails to rise despite measures taken to increase plasma volume, use of vasoactive substances should be considered.

Convulsions: Diazepam or barbiturates.

Warning: Diazepam or barbiturates may aggravate respiratory depression (especially in children), hypotension, and coma. However, barbiturates should not be used if drugs that inhibit monoamine oxidase have also been taken by the patient either in overdosage or in recent therapy (within 1 week).

Surveillance: Respiration, cardiac function (ECG monitoring), blood pressure, body temperature, pupillary reflexes, and kidney and bladder function should be monitored for several days.

Treatment of Blood Count Abnormalities: If evidence of significant bone marrow depression develops, the following recommendations are suggested: (1) stop the drug, (2) perform daily CBC, platelet, and reticulocyte counts, (3) do a bone marrow aspiration and trephine biopsy immediately and repeat with sufficient frequency to monitor recovery.

Special periodic studies might be helpful as follows: (1) white cell and platelet antibodies, (2) ^59Fe-ferrokinetic studies, (3) peripheral blood cell typing, (4) cytogenetic studies on marrow and peripheral blood, (5) bone marrow culture studies for colony-forming units, (6) hemoglobin electrophoresis for A2 and F hemoglobin, and (7) serum folic acid and B^12 levels.

A fully developed aplastic anemia will require appropriate, intensive monitoring and therapy, for which specialized consultation should be sought.

DOSAGE AND ADMINISTRATION

Monitoring of blood levels has increased the efficacy and safety of anticonvulsants (see PRECAUTIONS, Laboratory Tests). Dosage should be adjusted to the needs of the individual patients. A low initial daily dosage with gradual increase is advised. As soon as adequate control is achieved, the dosage may be reduced very gradually to the minimum effective level. Carbatrol may be taken with or without food. Carbatrol capsules may be swallowed whole or may be opened and all the beads sprinkled on a teaspoon of soft food such as applesauce. Make sure all of the food and medicine mixture is swallowed. Do not crush or chew Carbatrol capsules or the sprinkled beads.

Carbatrol is an extended-release formulation for twice a day administration. When converting patients from immediate release carbamazepine to Carbatrol extended-release capsules, the same total daily mg dose of carbamazepine should be administered. Following conversion to Carbatrol, patients should be closely monitored for seizure control. Depending on the therapeutic response after conversion, the total daily dose may need to be adjusted within the recommended dosing instructions.

Epilepsy (see INDICATIONS AND USAGE)

Adults and children over 12 years of age. Initial: 200 mg twice daily. Increase at weekly intervals by adding up to 200 mg/day until the optimal response is obtained. Dosage generally should not exceed 1000 mg per day in children 12-15 years of age, and 1200 mg daily in patients above 15 years of age. Doses up to 1600 mg daily have been used in adults. Maintenance: Adjust dosage to the minimum effective level, usually 800-1200 mg daily.

Children under 12 years of age: Children taking total daily dosages of immediate-release carbamazepine of 400 mg or greater may be converted to the same total daily dosage of Carbatrol extended-release capsules, using a twice daily regimen. Ordinarily, optimal clinical response is achieved at daily doses below 35 mg/kg. If satisfactory clinical response has not been achieved, plasma levels should be measured to determine whether or not they are in the therapeutic range. No recommendation regarding the safety of Carbatrol for use at doses above 35 mg/kg/24 hours can be made.

Combination Therapy: Carbatrol may be used alone or with other anticonvulsants. When added to existing anticonvulsant therapy, the drug should be added gradually while the other anticonvulsants are maintained or gradually decreased, except phenytoin, which may have to be increased (see PRECAUTIONS, Drug Interactions).

Trigeminal Neuralgia (see INDICATIONS AND USAGE)

Initial: On the first day, start with one 200 mg capsule. This daily dose may be increased by up to 200 mg/day every 12 hours only as needed to achieve freedom from pain. Do not exceed 1200 mg daily.

Maintenance: Control of pain can be maintained in most patients with 400-800 mg daily. However, some patients may be maintained on as little as 200 mg daily, while others may require as much as 1200 mg daily. At least once every 3 months throughout the treatment period, attempts should be made to reduce the dose to the minimum effective level or even to discontinue the drug.

HOW SUPPLIED

Carbatrol (carbamazepine) extended-release capsules is supplied in three dosage strengths.

100 mg-Two-piece hard gelatin capsule (bluish green opaque body and cap) printed with the Shire logo in white ink.

Supplied in bottles of 120........................... NDC 54092-171-12

200 mg-Two-piece hard gelatin capsule (light gray opaque body with bluish green opaque cap) printed with the Shire logo in white ink.

Supplied in bottles of 120 ............................NDC 54092-172-12

300 mg-Two-piece hard gelatin capsule (black opaque body with bluish green opaque cap) printed with the Shire logo in white ink.

Supplied in bottles of 120 ............................NDC 54092-173-12

Store at 25°C (77°F); excursions permitted to 15-30°C (59-86°F) [see USP controlled room temperature]. PROTECT FROM LIGHT AND MOISTURE.

To report SUSPECTED ADVERSE REACTIONS, contact Takeda Pharmaceuticals at 1-800-828-2088 or FDA at 1-800-FDA-1088 or www.fda.gov/medwatch

Distributed by:
Takeda Pharmaceuticals America, Inc.
Cambridge, MA 02142

CARBATROL is a registered trademark of Takeda Pharmaceuticals U.S.A., Inc.

© 2025 Takeda Pharmaceuticals U.S.A., Inc. All rights reserved.

Rev 6/2025

Medication Guide
CARBATROL® (CAR-BA-TROL)
(carbamazepine)
Extended-Release Capsules

Read this Medication Guide before you start taking CARBATROL and each time you get a refill. There may be new information. This information does not take the place of talking to your healthcare provider about your medical condition or treatment.

What is the most important information I should know about CARBATROL?

Do not stop taking CARBATROL without first talking to your healthcare provider.
Stopping CARBATROL suddenly can cause serious problems.

CARBATROL can cause serious side effects, including:

1. CARBATROL may cause rare but serious rashes that may lead to death. These serious skin reactions are more likely to happen within the first four months of CARBATROL treatment but may occur at later times. These reactions can happen in anyone, but are more likely in people of Asian descent. If you are of Asian descent you may need a genetic blood test before you take CARBATROL to see if you are at a higher risk for serious skin reactions with this medicine. Symptoms may include:

- skin rash
- hives
- sores in your mouth
- blistering or peeling of the skin

2. CARBATROL can also cause other types of allergic reactions or serious problems that may affect organs and other parts of your body such as your liver or blood cells. You may or may not have a rash when you get these types of reactions. Call your healthcare provider right away if you have any of these symptoms:

- swelling of your face, eyes, lips, or tongue
- trouble swallowing or breathing
- frequent fevers or fevers that do not go away
- frequent infections or an infection that does not go away
- unusual bruising or bleeding
- red or purple spots on your body
- severe fatigue or weakness
- unexpected muscle pain that does not go away
- swollen glands that do not go away
- yellowing of your skin or the whites of your eyes
- loss of appetite (anorexia) that does not go away
- nausea or vomiting that does not go away

These symptoms may be the first signs of a serious reaction. A healthcare provider should examine you to decide if you should continue taking CARBATROL.

3. Like other antiepileptic drugs, CARBATROL may cause suicidal thoughts or actions in a very small number of people, about 1 in 500.

Call your healthcare provider right away if you have any of these symptoms, especially if they are new, worse, or worry you:

- thoughts about suicide or dying
- attempt to commit suicide
- new or worse depression
- new or worse anxiety
- feeling agitated or restless
- panic attacks
- trouble sleeping (insomnia)
- new or worse irritability
- acting aggressive, being angry, or violent
- acting on dangerous impulses
- an extreme increase in activity and talking (mania)
- other unusual changes in behavior or mood

How can I watch for early symptoms of suicidal thoughts and actions?

- Pay attention to any changes, especially sudden changes, in mood, behaviors, thoughts, or feelings.
- Keep all follow-up visits with your healthcare provider as scheduled.
- Call your healthcare provider between visits as needed, especially if you are worried about symptoms.

Do not stop CARBATROL without first talking to a healthcare provider.

Stopping CARBATROL suddenly can cause serious problems.

Suicidal thoughts or actions can be caused by things other than medicines. If you have suicidal thoughts or actions, your healthcare provider may check for other causes.

What is CARBATROL?

CARBATROL is a medicine used to treat:

- certain types of seizures (partial, tonic-clonic, mixed)
- certain types of nerve pain (trigeminal and glossopharyngeal neuralgia).

CARBATROL is not a regular pain medicine and should not be used for aches or pains.

Who should not take CARBATROL?

Do not take CARBATROL if you:

- have a history of bone marrow depression
- are allergic to carbamazepine or any of the ingredients in CARBATROL. See the end of this Medication Guide for a complete list of ingredients in CARBATROL.
- take nefazodone
- take delavirdine
- are allergic to antidepressant medications called tricyclic (TCAs).
- have taken a medicine called Monoamine Oxidase Inhibitor (MAOI) in the last 14 days.

Ask your healthcare provider or pharmacist for a list of these medicines if you are not sure.

What should I tell my healthcare provider before taking CARBATROL?

Before you take CARBATROL, tell your healthcare provider if you:

- have or ever had heart problems
- have or ever had blood problems
- have or ever had liver or kidney problems
- have or ever had allergic reactions to medicines
- have or ever had increased pressure in your eye
- have or have had suicidal thoughts or actions, depression or mood problems
- have any other medical conditions
- drink grapefruit juice or eat grapefruit
- use birth control. CARBATROL may make your birth control less effective. Tell your healthcare provider if your menstrual bleeding changes while you take birth control and CARBATROL.
- are pregnant or plan to become pregnant. CARBATROL may harm your unborn baby. Tell your healthcare provider right away if you become pregnant while taking CARBATROL. You and your healthcare provider should decide if you should take CARBATROL while you are pregnant.
  - If you become pregnant while taking CARBATROL, talk to your healthcare provider about registering with the North American Antiepileptic Drug (NAAED) Pregnancy Registry. The purpose of this registry is to collect information about the safety of antiepileptic medicine during pregnancy. You can enroll in this registry by calling 1-888-233-2334.
- are breastfeeding or plan to breastfeed. CARBATROL passes into breast milk. You and your healthcare provider should discuss whether you should take CARBATROL or breastfeed. You should not do both.

Tell your healthcare provider about all the medicines you take, including prescription and non-prescription medicines, vitamins, and herbal supplements.

Taking CARBATROL with certain other medicines can cause side effects or affect how well they work. Do not start or stop other medicines without talking to your healthcare provider.

Know the medicines you take. Keep a list of them and show it to your healthcare provider and pharmacist when you get a new medicine.

How should I take CARBATROL?

- Take CARBATROL exactly as prescribed. Your doctor will tell you how much CARBATROL to take.
- Your healthcare provider may change your dose. Do not change your dose of CARBATROL without talking to your healthcare provider.
- Do not stop taking CARBATROL without first talking to your healthcare provider. Stopping CARBATROL suddenly can cause serious problems. Stopping seizure medicine suddenly in a patient who has epilepsy can cause seizures that will not stop (status epilepticus).
- Take CARBATROL with or without food.
- Do not crush, chew, or break CARBATROL capsules or the beads inside of the capsules. But, CARBATROL capsules can be opened and sprinkled over food such as a teaspoon of applesauce. Tell your healthcare provider if you can not swallow CARBATROL whole.
- If you take too much CARBATROL, call your healthcare provider or local Poison Control Center right away.

What should I avoid while taking CARBATROL?

- Do not drink alcohol or take other drugs that may make you sleepy or dizzy while taking CARBATROL until you talk to your healthcare provider. CARBATROL taken with alcohol or drugs may make your sleepiness or dizziness worse.
- Do not drive, or operate heavy machinery, or do other dangerous activities until you know how CARBATROL affects you. CARBATROL can slow your thinking and motor skills.

What are the possible side effects of CARBATROL?
See "What is the most important information I should know about CARBATROL?"

CARBATROL may cause other serious side effects including:

- Irregular heartbeat - symptoms include:
  - Fast, slow, or pounding heartbeat
  - Shortness of breath
  - Feeling lightheaded
  - Fainting
- Liver problems - symptoms include:
  - yellowing of your skin or the whites of your eyes
  - dark urine
  - pain on the right side of your stomach area (abdominal pain)
  - easy bruising
  - loss of appetite
  - nausea or vomiting

Get medical help right away if you have any of the symptoms listed above or listed in "What is the most important information I should know about CARBATROL".

The most common side effects of CARBATROL include:

- dizziness
- drowsiness
- problems with walking and coordination (unsteadiness)
- nausea
- vomiting

These are not all the side effects of CARBATROL. For more information, ask your healthcare provider or pharmacist.

Tell your healthcare provider if you have any side effect that bothers you or that does not go away.

Call your doctor for medical advice about side effects. You may report side effects to FDA at 1-800-FDA-1088.

How should I store CARBATROL?

- Store CARBATROL between 59°F to 86°F (15°C to 30°C).
- Keep CARBATROL out of the light.
- Keep CARBATROL capsules dry.

Keep CARBATROL and all medicines out of the reach of children.

General information about CARBATROL

Medicines are sometimes prescribed for purposes other than those listed in a Medication Guide. Do not use CARBATROL for a condition for which it was not prescribed. Do not give CARBATROL to other people, even if they have the same symptoms that you have. It may harm them.

This Medication Guide summarizes the most important information about CARBATROL. If you would like more information, talk with your healthcare provider. You can ask your pharmacist or healthcare provider for information about CARBATROL that is written for health professionals.

For more information go to www.carbatrol.com or call 1-800-828-2088.

What are the ingredients in CARBATROL?

Active ingredient: carbamazepine

Inactive ingredients: citric acid, colloidal silicon dioxide, lactose monohydrate, microcrystalline cellulose, polyethylene glycol, povidone, sodium lauryl sulfate, talc, triethyl citrate and Eudragit.

In addition:

- the 100 mg capsules contain gelatin-NF, FD&C Blue #2, Yellow Iron Oxide, and titanium dioxide and are imprinted with white ink
- the 200 mg capsules contain gelatin-NF, FD&C Red #3, FD&C Yellow #6, Yellow Iron Oxide, FD&C Blue #2, and titanium dioxide, and are imprinted with white ink
- the 300 mg capsules contain gelatin-NF, FD&C Blue #2, FD&C Yellow #6, Red Iron Oxide, Yellow Iron Oxide, and titanium dioxide, and are imprinted with white ink

This Medication Guide has been approved by the US Food and Drug Administration.

Distributed by:
Takeda Pharmaceuticals America, Inc.
Cambridge, MA 02142

CARBATROL is a registered trademark of Takeda Pharmaceuticals U.S.A., Inc.

© 2025 Takeda Pharmaceuticals U.S.A., Inc. All rights reserved.

Issued 6/2025

PRINCIPAL DISPLAY PANEL - 100 mg Capsule Bottle Label

NDC 54092-171-12

Carbatrol ®
(Carbamazepine)
Extended-Release
Capsules

120 Capsules

Rx only
Should not be used
with other carbamazepine
containing products.

100 mg

Takeda

Dispense the accompanying
Medication Guide to each patient.

PRINCIPAL DISPLAY PANEL - 200 mg Capsule Bottle Label

NDC 54092-172-12

Carbatrol ®
(Carbamazepine)
Extended-Release
Capsules

120 Capsules

Rx only
Should not be used
with other carbamazepine
containing products.

200 mg

Takeda

Dispense the accompanying
Medication Guide to each patient.

PRINCIPAL DISPLAY PANEL - 300 mg Capsule Bottle Label

NDC 54092-173-12

Carbatrol ®
(Carbamazepine)
Extended-Release
Capsules

120 Capsules

Rx only
Should not be used
with other carbamazepine
containing products.

300 mg

Takeda

Dispense the accompanying
Medication Guide to each patient.